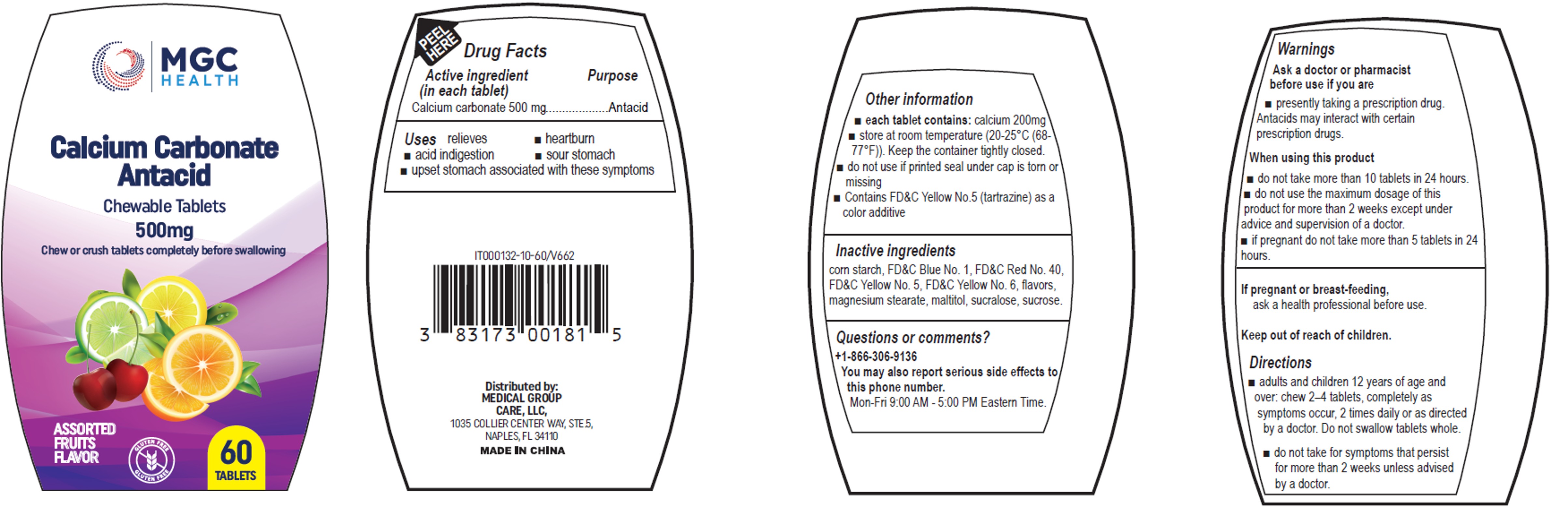 DRUG LABEL: MGC Health Calcium Carbonate Antacid
NDC: 83173-135 | Form: TABLET
Manufacturer: Medical Group Care LLC
Category: otc | Type: HUMAN OTC DRUG LABEL
Date: 20260108

ACTIVE INGREDIENTS: CALCIUM CARBONATE 500 mg/1 1
INACTIVE INGREDIENTS: STARCH, CORN; FD&C BLUE NO. 1; FD&C RED NO. 40; MAGNESIUM STEARATE; MALTITOL; SUCRALOSE; SUCROSE; FD&C YELLOW NO. 5; FD&C YELLOW NO. 6

MGC-Xiamen Antacid (500 mg) Assorted Fruits

Active ingredient (in each tablet)

Calcium carbonate 500 mg

Purpose

Antacid

Uses

relieves

- heartburn
- acid indigestion
- sour stomach
- upset stomach associated with these symptoms

Warnings

Ask a doctor or pharmacist before use if you are

- presently taking a prescription drug. Antacids may interact with certain prescription drugs.

When using this product

- do not take more than 10 tablets in 24 hours.
- do not use the maximum dosage of this product for more than 2 weeks except under advice and supervision of a doctor
- if pregnant do not take more than 5 tablets in 24 hours.

If pregnant or breast-feeding,

ask a health professional before use

Directions

- adults and children 12 years of age and over: chew 2-4 tablets, completely as symptoms occur, 2 times daily or as directed by a doctor. Do not swallow tablets whole.
- do not take for symptoms that persist for more than 2 weeks unless advised by a doctor.

Other information

- each tablet contains:calcium 200 mg
- store at room temperature (20-25°C (68-75°F)). Keep the container tightly closed.
- do not use if printed seal under cap is torn or missing
- Contains FD&C Yellow No. 5 (tartrazine) as a color additive

Inactive ingredients

Corn starch, FD&C Blue No.1, FD&C Red No. 40, FD&C Yellow No. 5 (tartrazine), flavors, magnesium stearate, maltitol, sucralose, sucrose

Questions or comments?

+1-866-306-9136
You may also report serious side effects to this phone
number.Mon-Fri 9:00 AM - 5:00 PM Eastern Time.